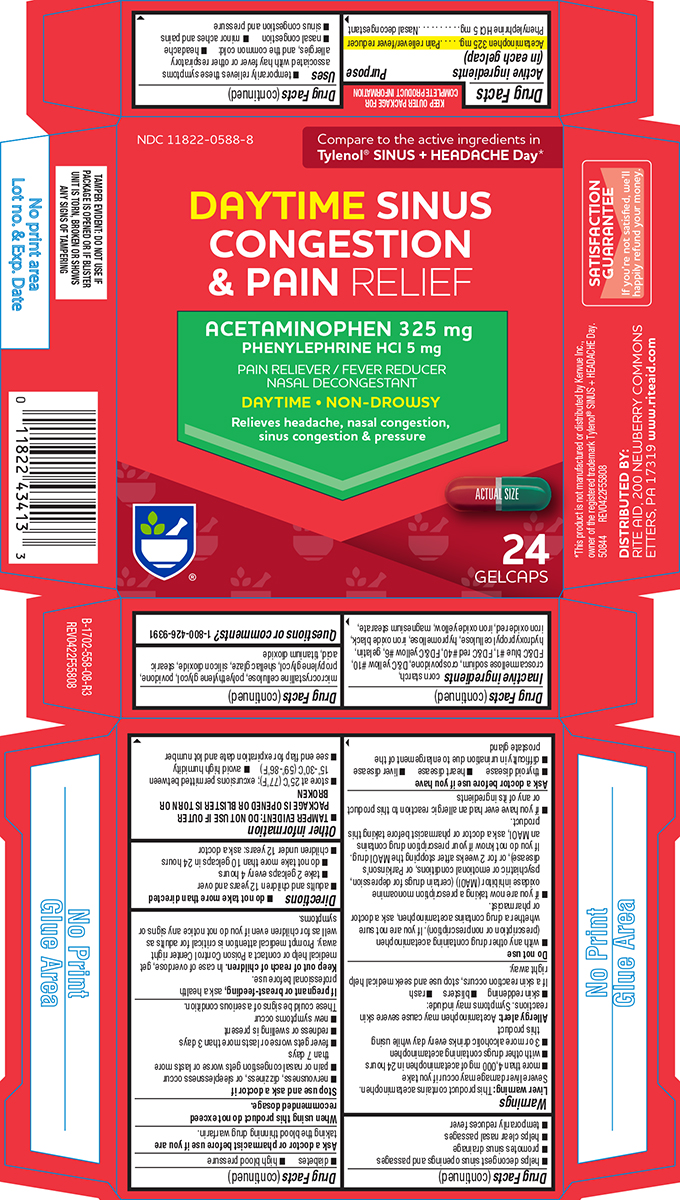 DRUG LABEL: Sinus Congestion and Pain Relief
NDC: 11822-0588 | Form: TABLET, COATED
Manufacturer: Rite Aid Corporation
Category: otc | Type: HUMAN OTC DRUG LABEL
Date: 20250130

ACTIVE INGREDIENTS: ACETAMINOPHEN 325 mg/1 1; PHENYLEPHRINE HYDROCHLORIDE 5 mg/1 1
INACTIVE INGREDIENTS: STARCH, CORN; CROSCARMELLOSE SODIUM; CROSPOVIDONE, UNSPECIFIED; D&C YELLOW NO. 10; FD&C BLUE NO. 1; FD&C RED NO. 40; FD&C YELLOW NO. 6; GELATIN, UNSPECIFIED; HYDROXYPROPYL CELLULOSE, UNSPECIFIED; HYPROMELLOSE, UNSPECIFIED; FERROSOFERRIC OXIDE; FERRIC OXIDE RED; FERRIC OXIDE YELLOW; MAGNESIUM STEARATE; MICROCRYSTALLINE CELLULOSE; POLYETHYLENE GLYCOL, UNSPECIFIED; POVIDONE, UNSPECIFIED; PROPYLENE GLYCOL; SHELLAC; SILICON DIOXIDE; STEARIC ACID; TITANIUM DIOXIDE

Rite Aid 44-558-Delisted

Active ingredients (in each gelcap)

Acetaminophen 325 mg
Phenylephrine HCl 5 mg

Purpose

Pain reliever/fever reducer
Nasal decongestant

Uses

- temporarily relieves these symptoms associated with hay fever or other respiratory allergies, and the common cold:
  - headache
  - sinus congestion and pressure
  - minor aches and pains
  - nasal congestion
- helps decongest sinus openings and passages
- promotes sinus drainage
- helps clear nasal passages
- temporarily reduces fever

Warnings

Liver warning: This product contains acetaminophen. Severe liver damage may occur if you take

- more than 4,000 mg of acetaminophen in 24 hours
- with other drugs containing acetaminophen
- 3 or more alcoholic drinks every day while using this product

Allergy alert: Acetaminophen may cause severe skin reactions. Symptoms may include:

- skin reddening
- blisters
- rash

If a skin reaction occurs, stop use and seek medical help right away.

Do not use

- with any other drug containing acetaminophen (prescription or nonprescription). If you are not sure whether a drug contains acetaminophen, ask a doctor or pharmacist.
- If you are now taking a prescription monoamine oxidase inhibitor (MAOI) (certain drugs for depression, psychiatric or emotional conditions, or Parkinson's disease), or for 2 weeks after stopping the MAOI drug. If you do not know if your prescription drug contains an MAOI, ask a doctor or pharmacist before taking this product.
- if you have ever had an allergic reaction to this product or any of its ingredients

Ask a doctor before use if you have

- liver disease
- thyroid disease
- heart disease
- diabetes
- difficulty in urination due to enlargement of the prostate gland
- high blood pressure

Ask a doctor or pharmacist before use if you are

taking the blood thinning drug warfarin.

When using this product

do not exceed recommended dosage.

Stop use and ask a doctor if

- nervousness, dizziness, or sleeplessness occur
- pain or nasal congestion gets worse or lasts more than 7 days
- new symptoms occur
- fever gets worse or lasts more than 3 days
- redness or swelling is present

These could be signs of a serious condition.

If pregnant or breast-feeding,

ask a health professional before use.

Keep out of reach of children.

In case of overdose, get medical help or contact a Poison Control Center right away. Prompt medical attention is critical for adults as well as for children even if you do not notice any signs or symptoms.

Directions

- do not take more than directed
- adults and children 12 years and over
  - take 2 gelcaps every 4 hours
  - do not take more than 10 gelcaps in 24 hours
- children under 12 years: ask a doctor

Other information

- TAMPER EVIDENT: DO NOT USE IF OUTER PACKAGE IS OPENED OR BLISTER IS TORN OR BROKEN
- avoid high humidity
- store at 25ºC (77ºF); excursions permitted between 15º-30ºC (59º-86ºF)
- see end flap for expiration date and lot number

Inactive ingredients

corn starch, croscarmellose sodium, crospovidone, D&C yellow #10, FD&C blue #1, FD&C red #40, FD&C yellow #6, gelatin, hydroxypropyl cellulose, hypromellose, iron oxide black, iron oxide red, iron oxide yellow, magnesium stearate, microcrystalline cellulose, polyethylene glycol, povidone, propylene glycol, shellac glaze, silicon dioxide, stearic acid, titanium dioxide

Questions or comments?

1-800-426-9391

Principal Display Panel

NDC 11822-0588-8

Compare to the active ingredients in
Tylenol® SINUS + HEADACHE Day*

DAYTIME SINUS
CONGESTION
& PAIN RELIEF

ACETAMINOPHEN 325 mg
PHENYLEPHRINE HCl 5 mg

PAIN RELIEVER / FEVER REDUCER
NASAL DECONGESTANT

DAYTIME • NON-DROWSY

Relieves headache, nasal congestion,
sinus congestion & pressure

ACTUAL SIZE

24
GELCAPS

TAMPER EVIDENT: DO NOT USE IF
PACKAGE IS OPENED OR IF BLISTER
UNIT IS TORN, BROKEN OR SHOWS
ANY SIGNS OF TAMPERING

*This product is not manufactured or distributed by Kenvue Inc.,
owner of the registered trademark Tylenol® SINUS + HEADACHE Day.
50844 REV0422F55808

DISTRIBUTED BY:
RITE AID, 200 NEWBERRY COMMONS
ETTERS, PA 17319 www.riteaid.com

SATISFACTION
GUARANTEE
If you're not satisfied, we'll
happily refund your money.

Rite Aid 44-558